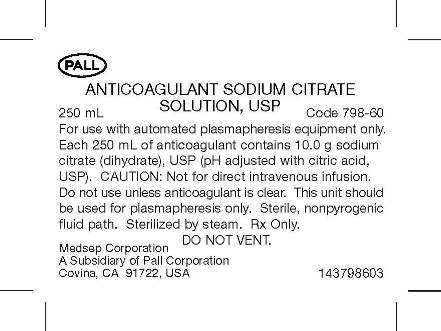 DRUG LABEL: Anticoagulant Sodium Citrate
NDC: 62646-798 | Form: SOLUTION
Manufacturer: Medsep Corporation
Category: prescription | Type: HUMAN PRESCRIPTION DRUG LABEL
Date: 20110520

ACTIVE INGREDIENTS: SODIUM CITRATE 10 g/250 mL
INACTIVE INGREDIENTS: WATER

Anticoagulant Sodium Citrate Solution, USP
Code 798-60

ANTICOAGULANT SODIUM CITRATE SOLUTION, USP

Sterile, non-pyrogenic fluid path. Sterilized by steam.

Rx only.

250 ml volume bag.

Store at room temperature.

INDICATIONS AND USAGE

For use with automated plasmapheresis equipment only. Use according to equipment manufacturer’s instructions. This unit should be used for plasmapheresis only.

WARNINGS

Not for direct intravenous infusion.

DO NOT VENT.

Avoid excessive heat. Protect from freezing.

GENERAL PRECAUTIONS

Do not use unless solution is clear and no leaks are detected.

Discard unused portion.

HOW SUPPLIED

Single Use Container.

INFORMATION FOR PATIENTS

Medsep Corporation, A Subsidiary of Pall Corp., Covina, CA 91722, USA

Visit us at www.pall.com/medical

For Pall customer service, call: 1.800.645.6578

CONTAINER TEXT DISPLAYED

Anticoagulant Sodium Citrate Bag Text

ANTICOAGULANT SODIUM CITRATE SOLUTION, USP

250 mL Code 798-60

For use with automated plasmapheresis equipment only. Each 250 mL of anticoagulant contains 10.0 g sodium citrate (dihydrate), USP (pH adjusted with citric acid, USP).

CAUTION: Not for direct intravenous infusion.

Do not use unless anticoagulant is clear. This unit should be used for plasmapheresis only. Sterile, nonpyrogenic fluid path. Sterilized by steam. Rx Only.

DO NOT VENT.

PACKAGE LABEL

Issued August 2010, 147798603